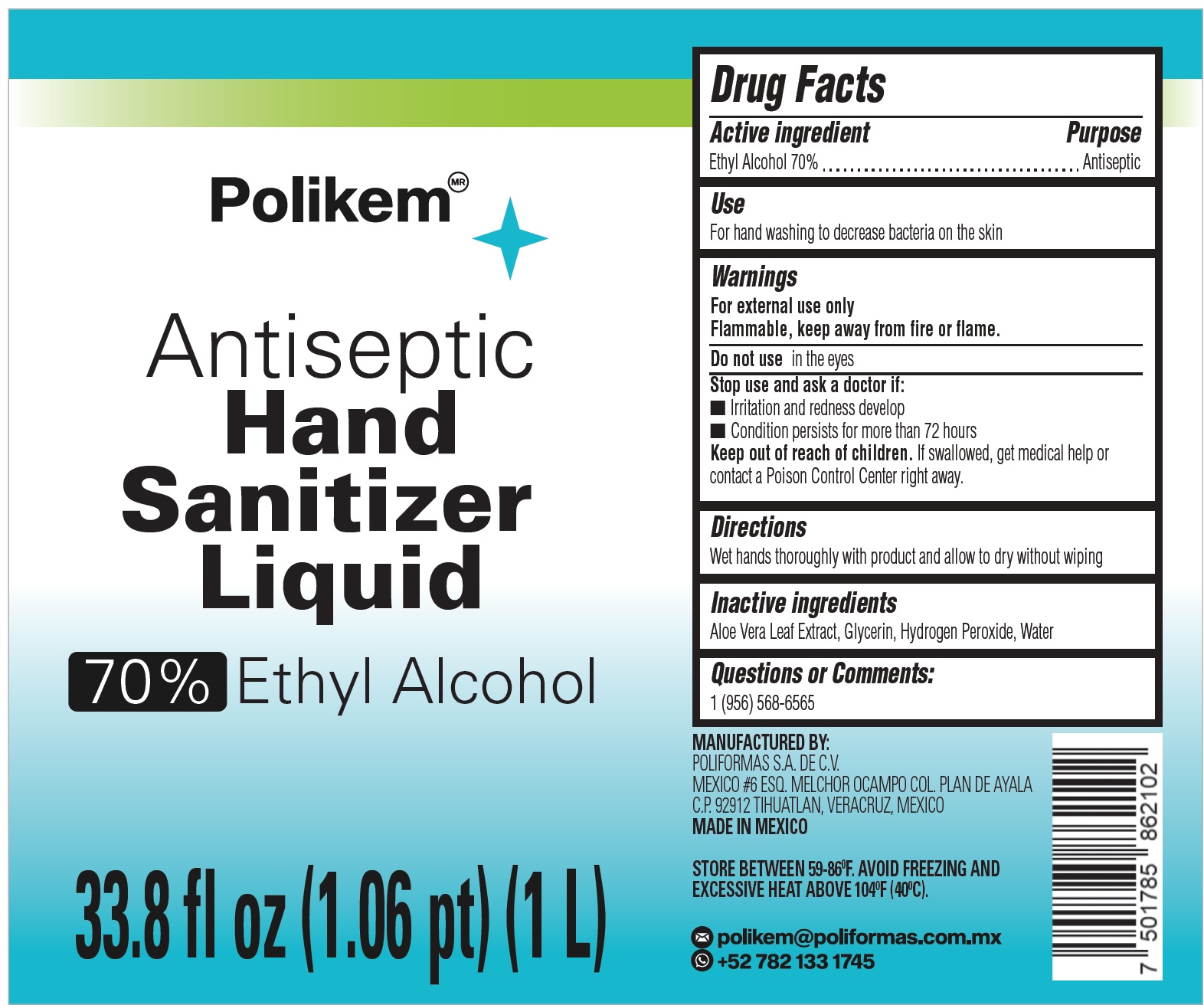 DRUG LABEL: Antiseptic Hand Sanitizer
NDC: 90097-000 | Form: LIQUID
Manufacturer: Poliformas S.A. de C.V.
Category: otc | Type: HUMAN OTC DRUG LABEL
Date: 20200812

ACTIVE INGREDIENTS: ALCOHOL 0.7 mL/1 mL
INACTIVE INGREDIENTS: ALOE VERA LEAF; GLYCERIN; HYDROGEN PEROXIDE; WATER

Antiseptic Hand Sanitizer

Active ingredient

Ethyl Alcohol 70%

Purpose

Antiseptic

Use

For hand washing to decrease bacteria on the skin

Warnings

For external use only
Flammable, keep away from fire or flame.

Do not use

in the eyes

Stop use and ask a doctor if:

- Irritation and redness develop
- Condition persists for more than 72 hours

Keep out of reach of children.

If swallowed, get medical help or contact a Poison Control Center right away.

Directions

Wet hands thoroughly with product and allow to dry without wiping

Inactive ingredients

Aloe Vera Leaf Extract, Glycerin, Hydrogen Peroxide, Water

Questions or Comments:

1 (956) 568-6565